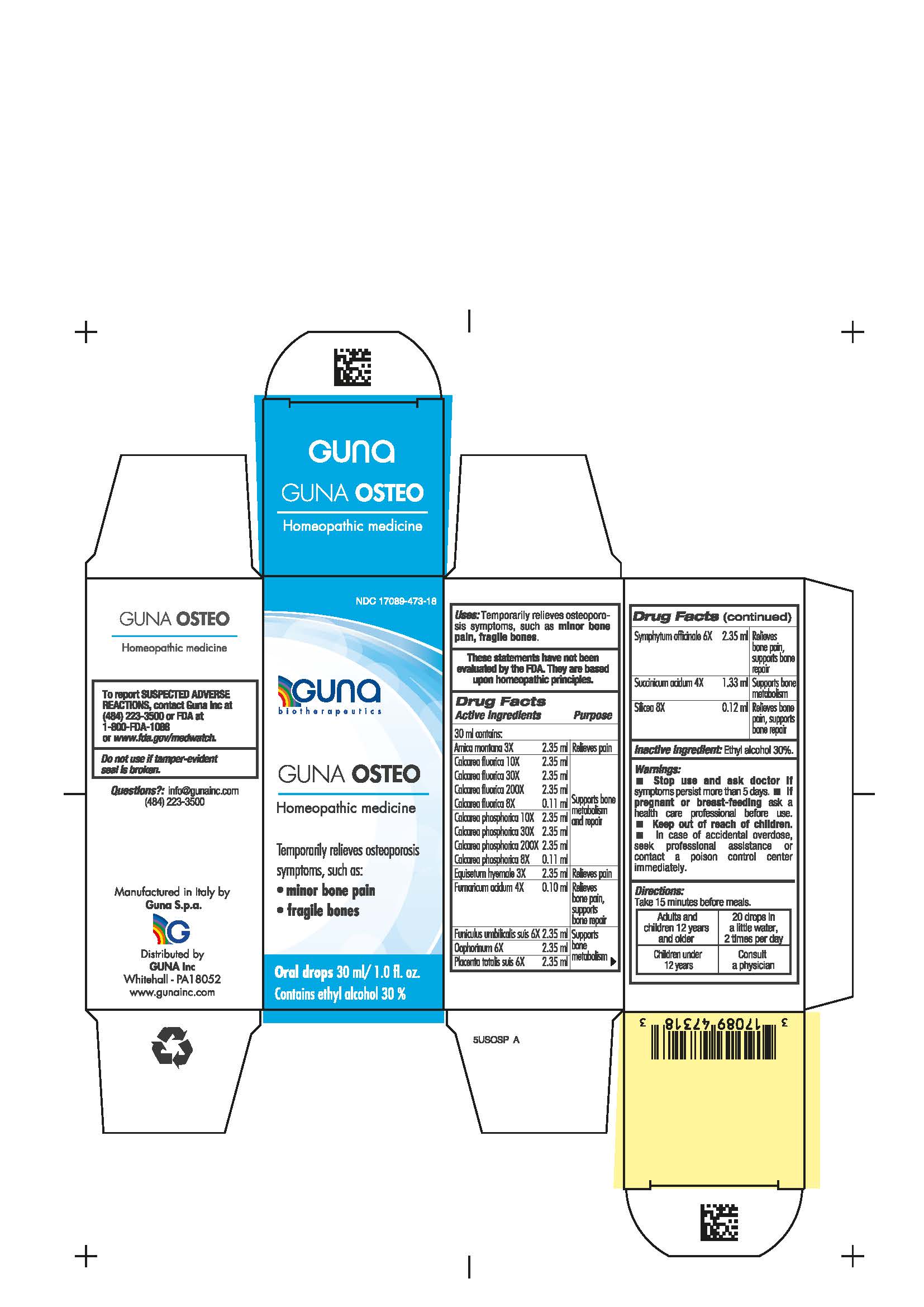 DRUG LABEL: GUNA OSTEO
NDC: 17089-473 | Form: SOLUTION/ DROPS
Manufacturer: Guna spa
Category: homeopathic | Type: HUMAN OTC DRUG LABEL
Date: 20210217

ACTIVE INGREDIENTS: ARNICA MONTANA ROOT 3 [hp_X]/30 mL; FUMARIC ACID 4 [hp_X]/30 mL; SUS SCROFA UMBILICAL CORD 6 [hp_X]/30 mL; SUS SCROFA OVARY 6 [hp_X]/30 mL; SUS SCROFA PLACENTA 6 [hp_X]/30 mL; COMFREY ROOT 6 [hp_X]/30 mL; SUCCINIC ACID 4 [hp_X]/30 mL; SILICON DIOXIDE 8 [hp_X]/30 mL; CALCIUM FLUORIDE 8 [hp_X]/30 mL; CALCIUM PHOSPHATE 8 [hp_X]/30 mL; EQUISETUM HYEMALE 3 [hp_X]/30 mL
INACTIVE INGREDIENTS: ALCOHOL 9 mL/30 mL

GUNA OSTEO

INDICATIONS AND USAGE

Take 15 minutes before meals

Inactive ingredient: Ethyl alcohol 30%.

QUESTIONS

Questions?: info@gunainc.com (484) 223-3500

DIRECTIONS

Adults and children 12 years and older 20 drops in a little water, 2 times per day
Children under 12 years of age consult a physician

WARNINGS

Keep out of reach of children

PREGNANCY

If pregnant or breast-feeding ask a health care professional before use

WARNINGS

Stop use and ask doctor if symptoms persist more than 5 days.
If pregnant or breast-feeding ask a health care professional before use.
Keep out of reach of children. In case of accidental overdose, seek professional assistance or contact a Poison Control Center immediately.
Contains ethyl alcohol 30%

USES

Temporarily relieves osteoporosis symptoms, such as:

- minor bone pain.
- fragile bones.

ACTIVE INGREDIENTS/PURPOSE

Arnica montana 3X Relieves pain

Calcarea fluorica 8X, 10X, 30X, 200X Supports bone metabolism and repair

Calcarea phosphorica 8X, 10X, 30X, 200X Supports bone metabolism and repair

Equisetum hyemale 3X Relieves pain

Fumaricum acidum 4X Relieves bone pain, supports bone repair

Funiculus umbilicalis suis 6X Supports bone metabolism

Oophorinum 6X Supports bone metabolism

Placenta totalis suis 6X Supports bone metabolism

Symphytum officinale 6X Relieves bone pain, supports bone repair

Succinicum acidum 4X Supports bone metabolism

Silicea 8X Relieves bone pain, supports bone repair